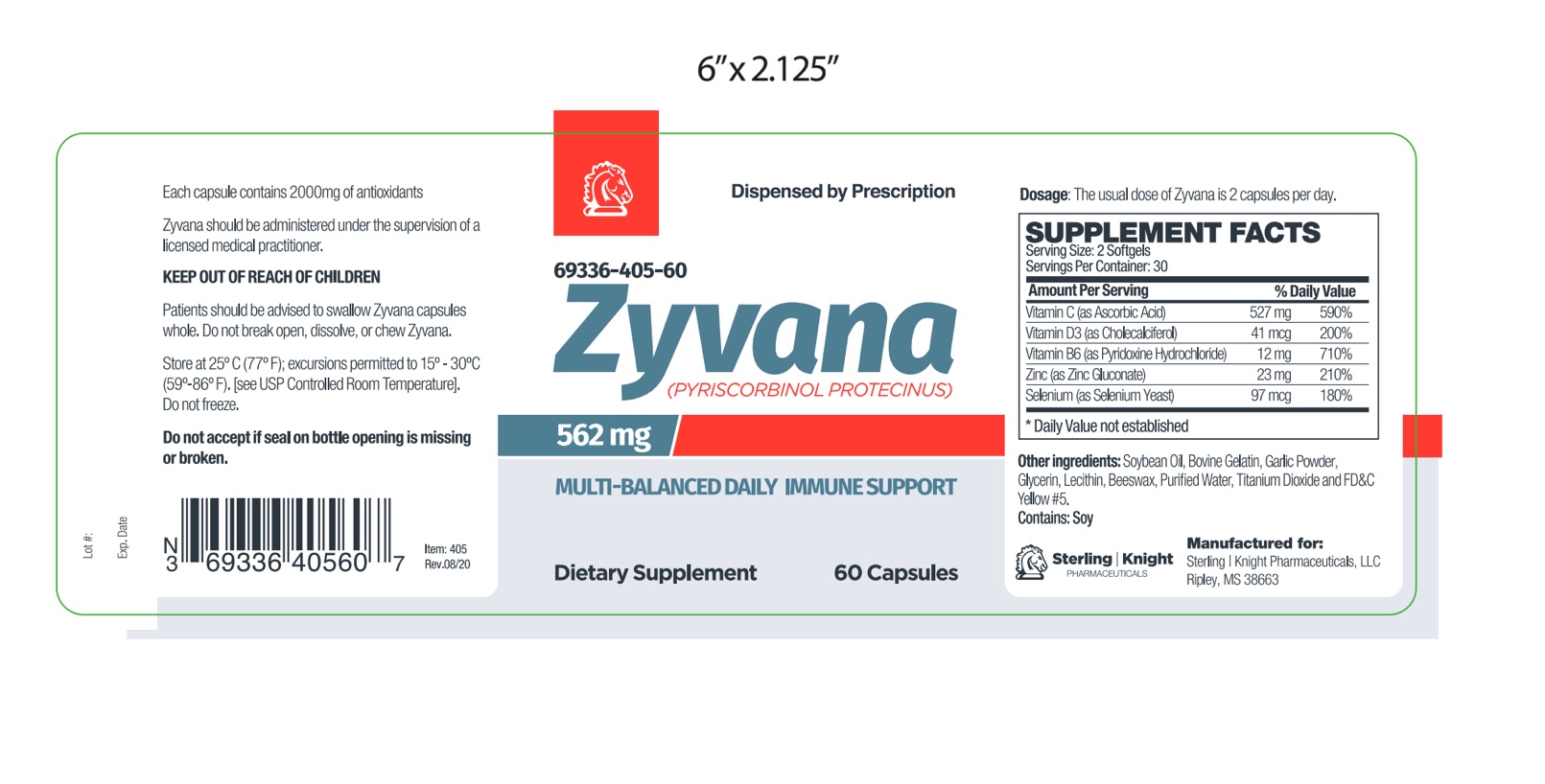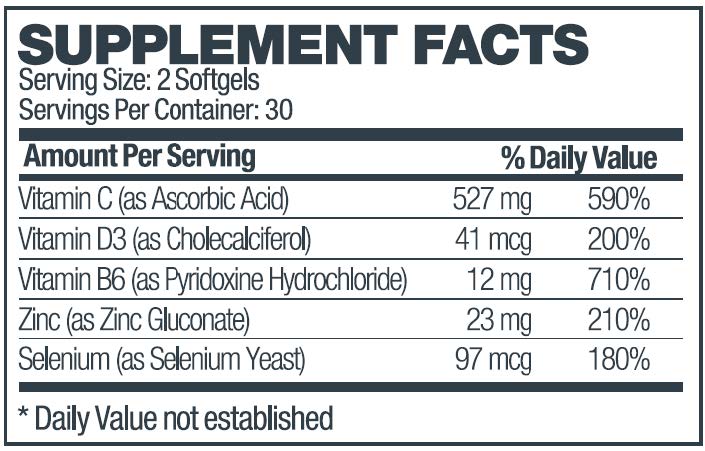 DRUG LABEL: Zyvana
NDC: 69336-405 | Form: CAPSULE
Manufacturer: Sterling-Knight Pharmaceuticals, LLC
Category: prescription | Type: HUMAN PRESCRIPTION DRUG LABEL
Date: 20210222

ACTIVE INGREDIENTS: ASCORBIC ACID 527 mg/1 1; CHOLECALCIFEROL 0.041 mg/1 1; PYRIDOXINE HYDROCHLORIDE 12 mg/1 1; ZINC GLUCONATE 23 mg/1 1; SELENIUM 0.097 mg/1 1
INACTIVE INGREDIENTS: SOYBEAN OIL; GELATIN; GARLIC; GLYCERIN; LECITHIN, SOYBEAN; PEG-8 BEESWAX; WATER; TITANIUM DIOXIDE; FD&C YELLOW NO. 5

Zyvana Capsules
Multi-Balanced Daily Immune Support
Dietary Supplement
Dispense by Prescription

DESCRIPTION

Zyvana is an orally administered prescription dietary supplement formulation.

Zyvana should be administered under the supervision of a licensed medical practitioner.

Other Ingredients: Soybean Oil, Gelatin (bovine), Garlic Powder, Glycerin, Lecithin, Beeswax, Purified Water, Titanium Dioxide, FD&C Yellow #5.

INDICATIONS AND USAGE

Zyvana is an orally administered prescription dietary supplement formulation for the management of suboptimal nutritional status in patients where advanced supplementation is required and nutritional supplementation in physiologically stressful conditions for maintenance of good health is needed.

WARNINGS AND PRECAUTIONS:

This product is contraindicated in patients with a known hypersensitivity to any of the ingredients.Zyvana should only be used under the direction and supervision of a licensed medical practitioner. Use with caution in patients that may have a medical condition, are pregnant, lactating, trying to conceive, under the age of 18, or taking medications.

DOSAGE AND ADMINISTRATION

The usual dose of Zyvana is 2 capsules per day.The daily dose may be taken as a single dose of 2 capsules or 1 capsule twice daily.

HOW SUPPLIED SECTION

Zyvana is supplied as yellow softgel capsule printed with 405 dispensed in white HDPE plastic bottles of 60ct. 69336-405-60

STORAGE

Store at controlled room temperature 15°-30°C (59°F-86°F). Keep in cool dry place. Call your doctor about side effects. You may report side effects to FDA at 1-800-FDA-1088. KEEP THIS OUT OF THE REACH OF CHILDREN.

Reserved for Professional Recommendation

All prescriptions using this dietary supplement product shall be pursuant to state statutes as applicable. This is not an Orange Book product. This product may be administered under a physician’s supervision. There are no implied or explicit claims on therapeutic equivalence.

PACKAGE LABEL.PRINCIPAL DISPLAY PANEL

Manufactured for:

Sterling-Knight Pharmaceuticals, LLC

Ripley, MS 38663

Item 40560

Rev. 0920-1